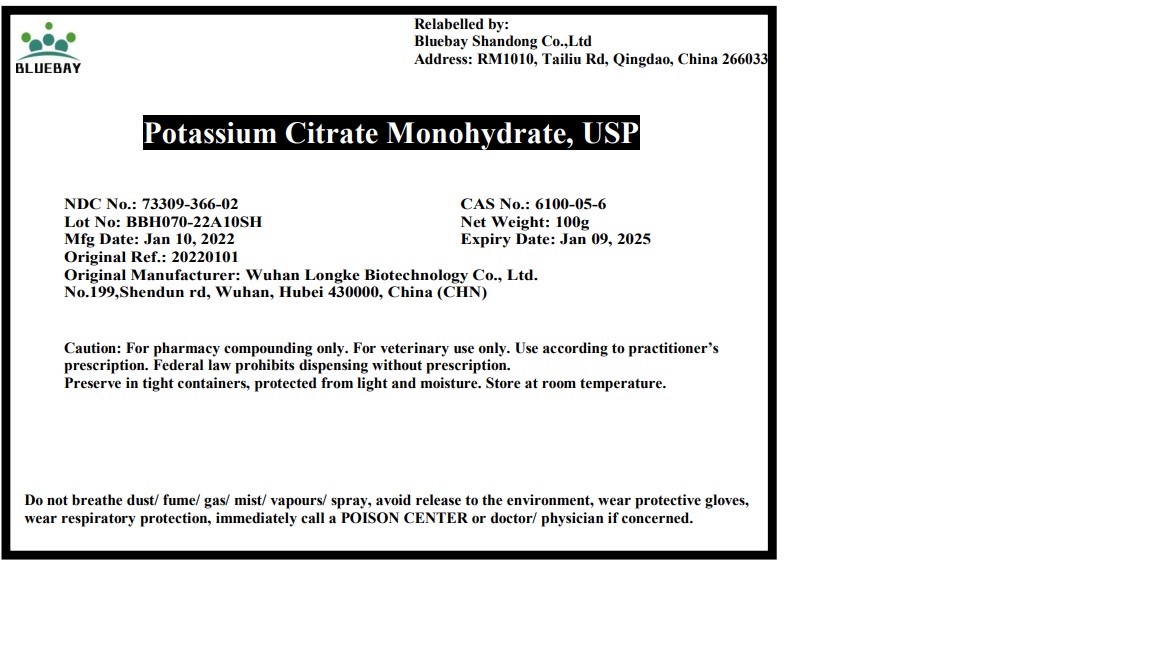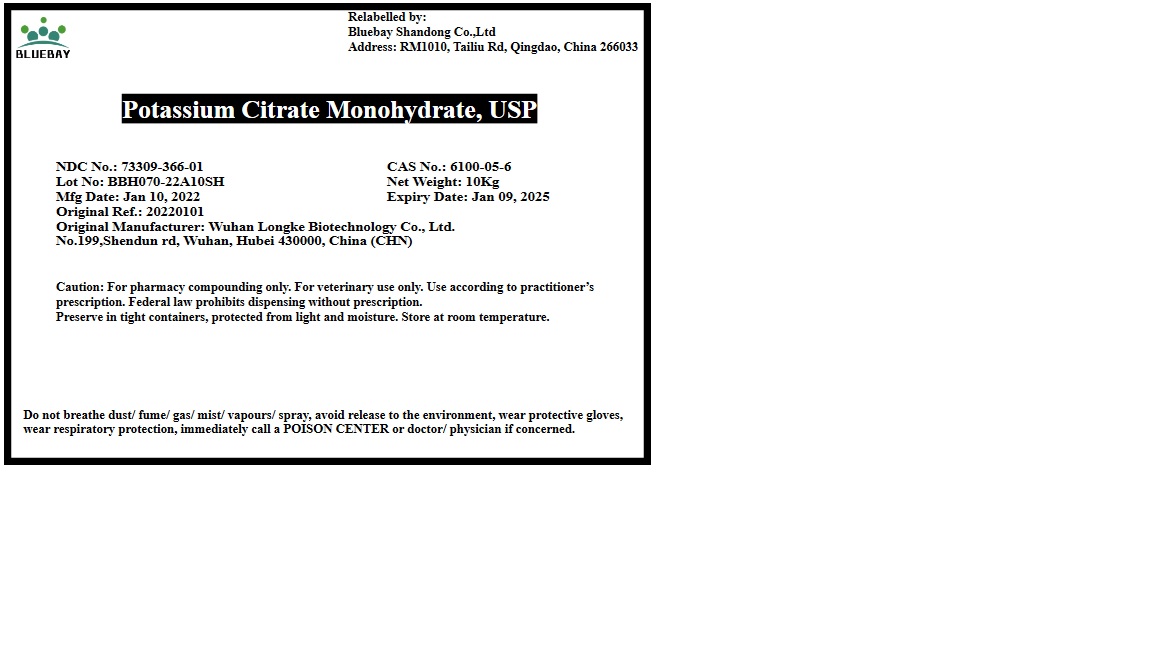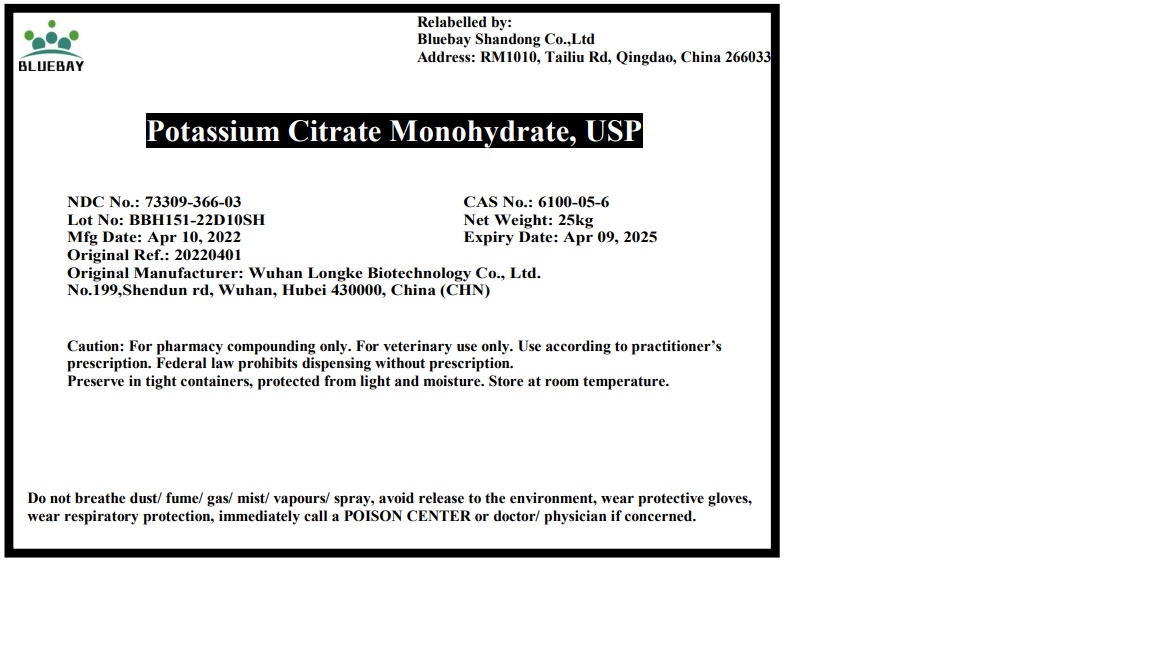 DRUG LABEL: potassium citrate monohydrate
NDC: 73309-366 | Form: POWDER
Manufacturer: BLUEBAY SHANDONG CO.,LTD
Category: other | Type: BULK INGREDIENT - ANIMAL DRUG
Date: 20220419

ACTIVE INGREDIENTS: POTASSIUM CITRATE 1 g/1 g

potassium citrate monohydrate